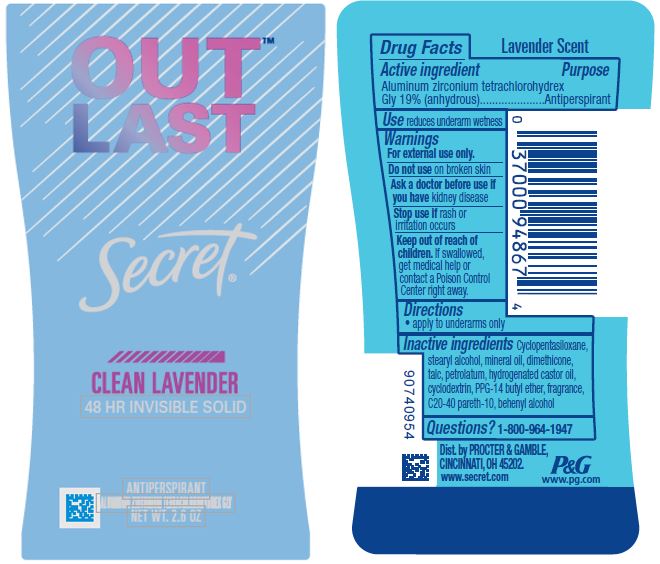 DRUG LABEL: Secret Outlast Clean Lavender Invisible
NDC: 69423-469 | Form: STICK
Manufacturer: The Procter & Gamble Manufacturing Company
Category: otc | Type: HUMAN OTC DRUG LABEL
Date: 20200526

ACTIVE INGREDIENTS: ALUMINUM ZIRCONIUM TETRACHLOROHYDREX GLY 19 g/100 g
INACTIVE INGREDIENTS: C20-40 PARETH-10; HYDROGENATED CASTOR OIL; CYCLOMETHICONE 5; STEARYL ALCOHOL; PPG-14 BUTYL ETHER; PETROLATUM; TALC; MINERAL OIL; DOCOSANOL; BETADEX; DIMETHICONE

Secret Outlast Clean Lavender Invisible Solid

Drug Facts

Active ingredient

Aluminum zirconium tetrachlorohydrex Gly 19% (anhydrous)

Purpose

Antiperspirant

Use

reduces underarm wetness

Warnings

For external use only.

Do not use on broken skin

Ask a doctor before use if you have kidney disease

Stop use if rash or irritation occurs

Keep out of reach of children. If swallowed, get medical help or contact a Poison Control Center right away.

Directions

- apply to underarms only

Inactive ingredients

Cyclopentasiloxane, stearyl alcohol, mineral oil, dimethicone, talc, petrolatum, hydrogenated castor oil, cyclodextrin, PPG-14 butyl ether, fragrance, C20-40 pareth-10, behenyl alcohol

Questions?

1-800-964-1947

Dist. by PROCTER & GAMBLE,
CINCINNATI, OH 45202.

PRINCIPAL DISPLAY PANEL - 73 g Canister Label

Secret

Outlast

CLEAN LAVENDER

48 HR INVISIBLE SOLID

ALUMINUM ZIRCONIUM TETRACHLOROHYDREX GLY

ANTIPERSPIRANT

NET WT. 2.6 OZ